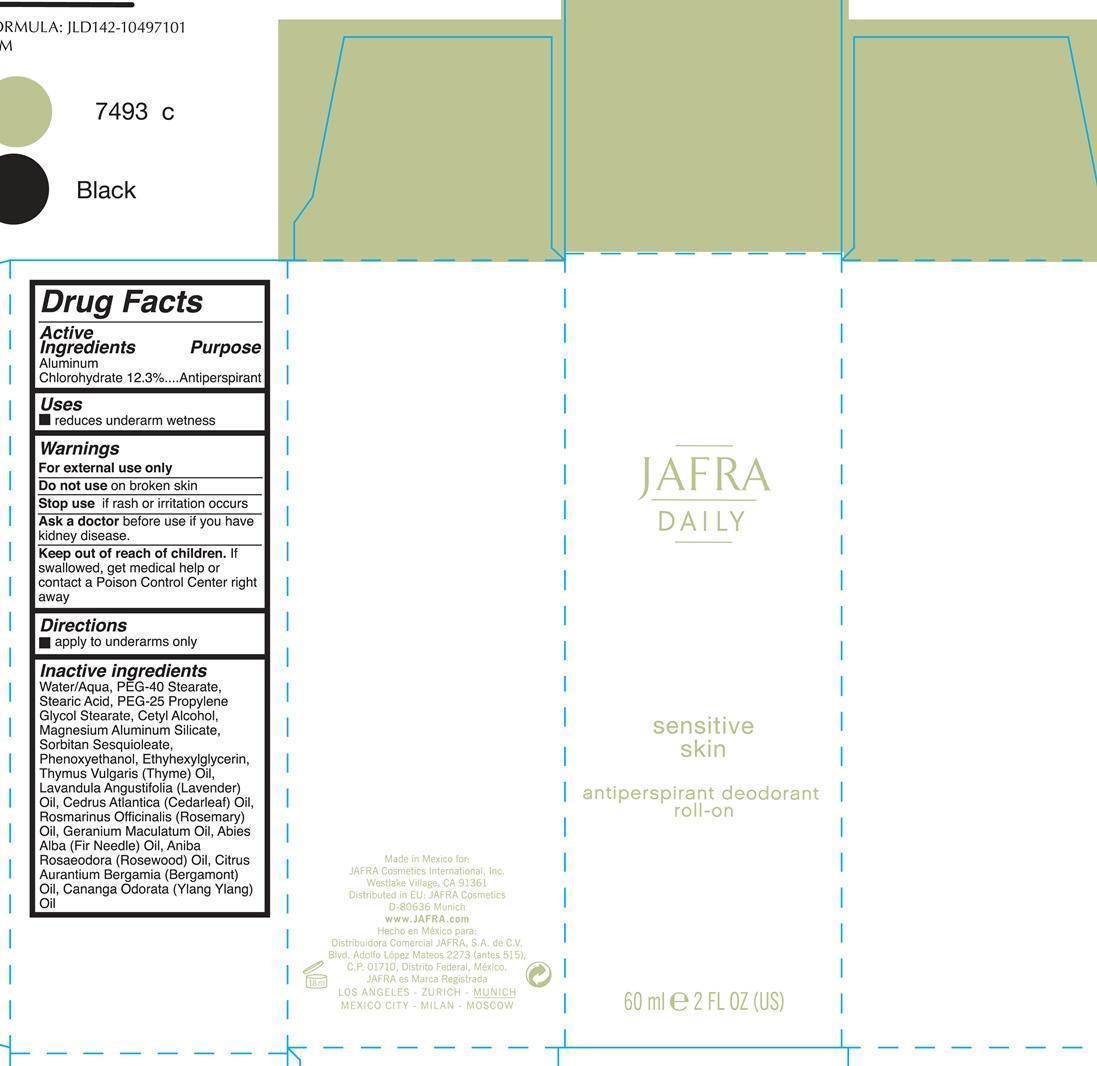 DRUG LABEL: Sensitive Skin antiperspirant deodorant  roll-on
NDC: 68828-197 | Form: LIQUID
Manufacturer: Jafra cosmetics International
Category: otc | Type: HUMAN OTC DRUG LABEL
Date: 20190522

ACTIVE INGREDIENTS: ALUMINUM CHLOROHYDRATE 12.3 g/100 mL
INACTIVE INGREDIENTS: WATER; PEG-40 STEARATE; STEARIC ACID; PEG-25 PROPYLENE GLYCOL STEARATE; GLYCOL STEARATE; CETYL ALCOHOL; MAGNESIUM ALUMINUM SILICATE; SORBITAN SESQUIOLEATE; PHENOXYETHANOL; ETHYLHEXYLGLYCERIN; THYME OIL; LAVENDER OIL; CEDAR LEAF OIL; ROSEMARY OIL; GERANIUM MACULATUM ROOT OIL; ABIES ALBA LEAF OIL; ROSEWOOD OIL; BERGAMOT OIL; CANANGA OIL

Jafra Daily Sensitive Skin Antiperspirant deodorant roll-on

Active Ingredients Purpose

Aluminum Chlorohydrate 12.3 % Antiperspirant

Uses

reduces underarm wetness

keep out of reach of children. If swallowed, get medical help or contact a Poison Control Center right away.

Stop use if rash or irritation occur

Warnings

For external use only

Do not use on Broken Skin

Ask a doctor before use if you have kidney disease.

Directions

apply to underarms only

Inactive ingredients

Water/Aqua, PEG-40 Stearate, Stearic Acid, PEG-25 Propylene Glycol Stearate, Cetyl Alcohol, Magnesium Aluminum Silicate, Sorbitan Sesqiolate Phenoxyethanol, Ethylhexylglycerin, Thymus Vulgaris (Thyme) Oil, Lavandula Angustifolia (Lavender) Oil, Cedrus Atlantica (cedarleaf) Oil, Rosmarinus Officinalis (Rosemary) Oil, Geranium Maculatum Oil, Abies Alba (Fir Needle) Oil, Aniba Roseadora (Rosewood) Oil, Citrus Aurantium Bergamia (Bergamont) Oil, Cananga Odorata (Ylang Ylang) Oil.

PACKAGE LABEL

Jafra

Daily
Sensitive Skin

Antiperspirant deodorant roll-on

60ml 2 FL OZ (US)